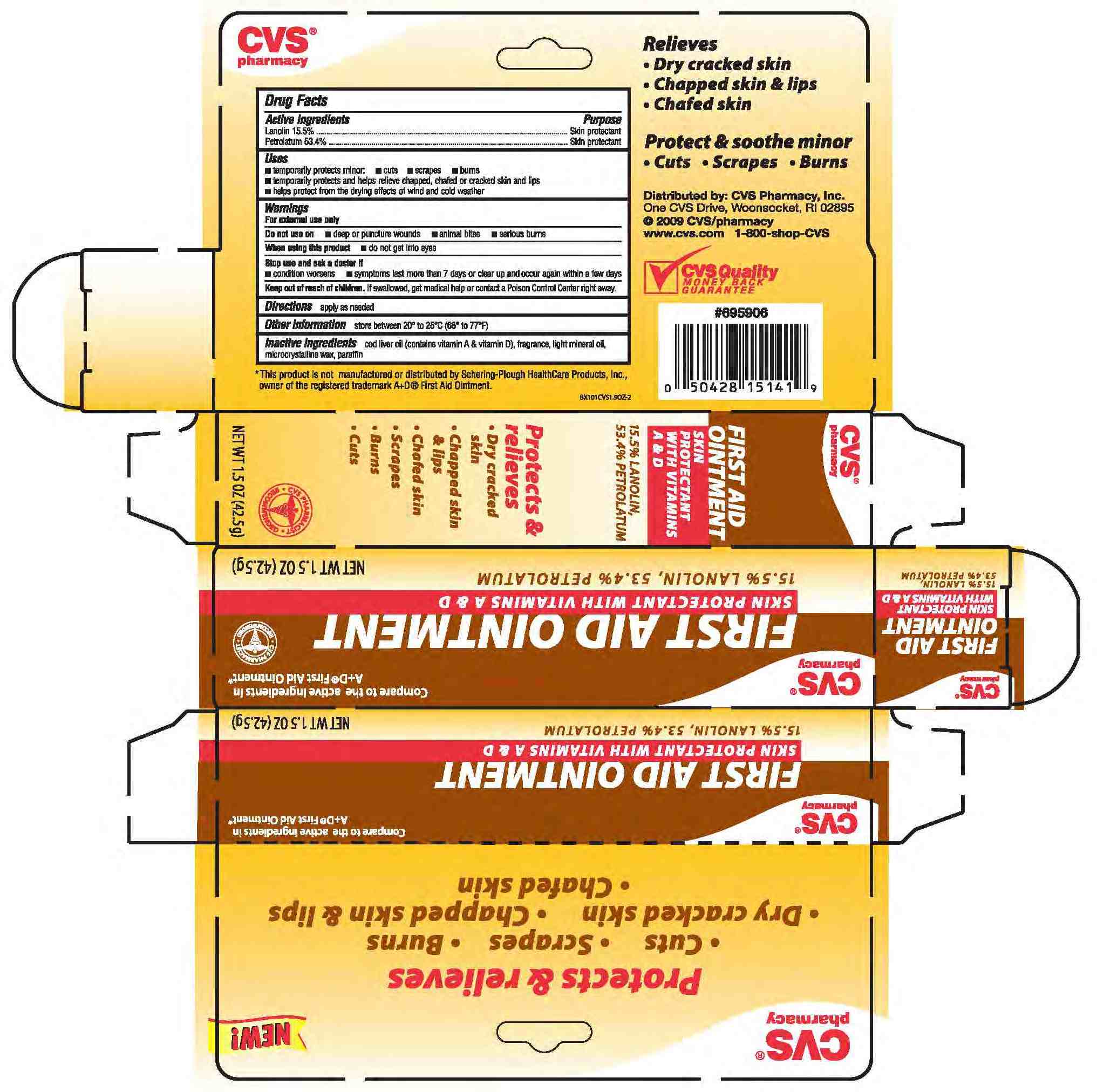 DRUG LABEL: PETROLATUM, LANOLIN
NDC: 59779-068 | Form: OINTMENT
Manufacturer: CVS
Category: otc | Type: HUMAN OTC DRUG LABEL
Date: 20110216

ACTIVE INGREDIENTS: PETROLATUM .534 g/1 g; LANOLIN .155 g/1 g
INACTIVE INGREDIENTS: PARAFFIN ; MICROCRYSTALLINE WAX; MINERAL OIL; COD LIVER OIL; CARROT SEED OIL

drug facts

Active ingredients Purpose
Lanolin 15.5%..>>>>...................................Skin Protectant
Petrolatum 53.4%.......................................Skin protectant

Active ingredients Purpose
Lanolin 15.5%..>>>>...................................Skin Protectant
Petrolatum 53.4%.......................................Skin protectant
______________________________________
Uses
- temporarily protects minor: - cuts - scrapes - burns
- temporarliy protects and helps relieved chapped, chafed or cracked skin and lips
- helps protect from the drying effects of wind and cold weather

KEEP OUT OF REACH OF CHILDREN

Keep out of the reach of children. If swallowed, get medical help or contact
a Poison Control Center right away.

Uses
- temporarily protects minor: - cuts - scrapes - burns
- temporarliy protects and helps relieved chapped, chafed or cracked skin and lips
- helps protect from the drying effects of wind and cold weather

Warnings
For external use only.
_______________________________
Do not use on:
- Deep or puncture wounds - animal bites - serious burns
_______________________________
When using this product - Do not get into eyes.
_______________________________
Stop use and ask a doctor if:
-condition worsens -symptoms last more than 7 days or clear
up and occur again within a few days
__________________________________
Keep out of reach of Children. If swallowed, get medical help or
contact a Poison Control Center right away

Directions
- apply as needed
________________________________
Other information
Store between 20 degrees to 25 degrees C (68 degrees to 77 degrees F)

INACTIVE INGREDIENT

Inactive Ingredients cod liver oil (contains vitamin A and vitamin D), fragrance, light mineral oil, microcrystalline wax, paraffin.